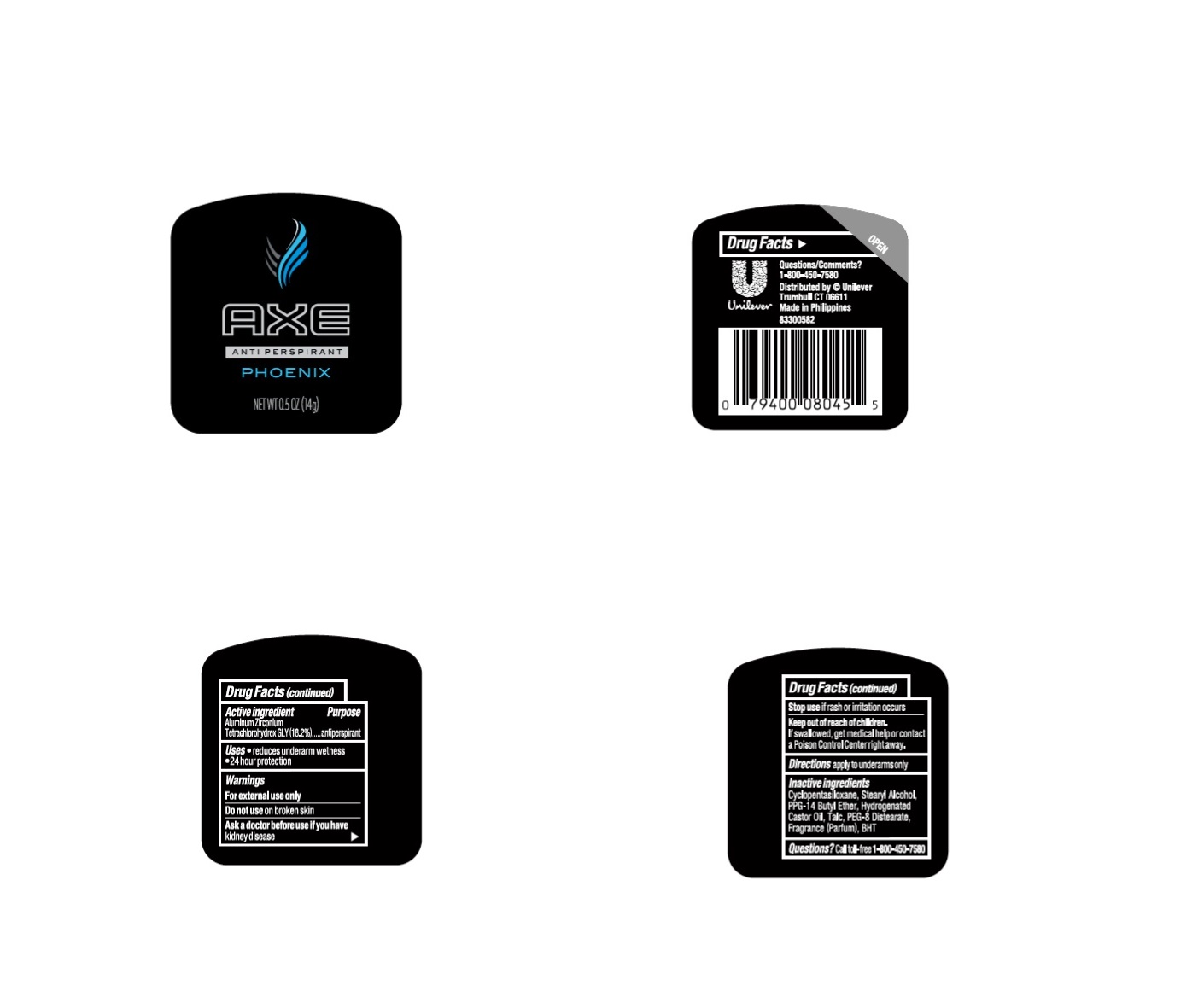 DRUG LABEL: Axe
NDC: 64942-2352 | Form: STICK
Manufacturer: Conopco Inc. d/b/a Unilever
Category: otc | Type: HUMAN OTC DRUG LABEL
Date: 20241003

ACTIVE INGREDIENTS: ALUMINUM ZIRCONIUM TETRACHLOROHYDREX GLY 18.2 g/100 g
INACTIVE INGREDIENTS: CYCLOMETHICONE 5; PPG-14 BUTYL ETHER; STEARYL ALCOHOL; HYDROGENATED CASTOR OIL; PEG-8 DISTEARATE; TALC; BUTYLATED HYDROXYTOLUENE

Axe Phoenix Antiperspirant

Active ingredient

Aluminum Zirconium Tetrachlorohydrex GLY(18.2%)

PURPOSE

Purposeanti-perspirant

Uses
·reduces underarm wetness
·24 hour protection

Warnings
For external use only

Do not use on broken skin

Ask a doctor before use if you havekidney disease

Stop useif rash or irritation occurs

Keep out of reach of children. If swallowed, get medical help or contact a Poison Control Center right away.

Directions
· apply to underarms only
·turn dial to raise product
·to ensure product appears clear on skin, do not overapply
·replace cap

Inactive ingredients

Cyclopentasiloxane, PPG-14 Butyl Ether, Stearyl Alcohol, Hydrogenated Castor Oil, PEG-8 Distearate, Talc, Fragrance (Parfum), BHT.

Questions?

Call toll-free 1-800-450-7580